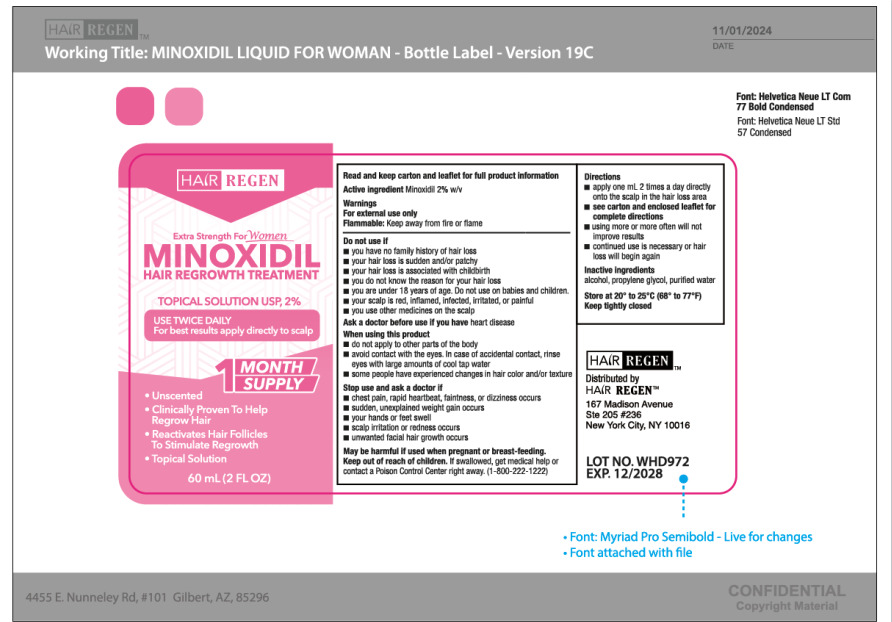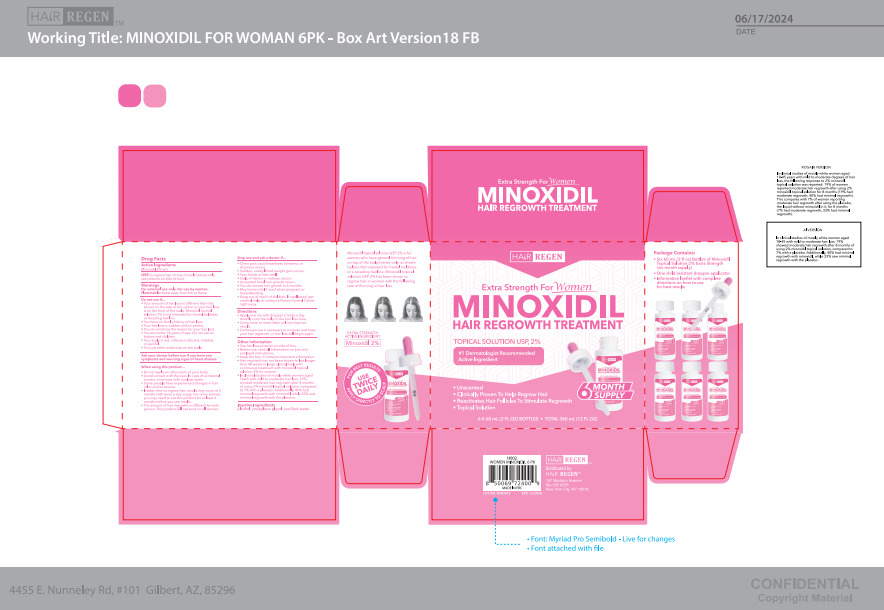 DRUG LABEL: HAIR REGEN HAIR REGROWTH TREATMENT
NDC: 84232-004 | Form: LIQUID
Manufacturer: YIWU YIZHOU TRADING CO.,LTD
Category: otc | Type: HUMAN OTC DRUG LABEL
Date: 20250108

ACTIVE INGREDIENTS: MINOXIDIL 2 g/100 mL
INACTIVE INGREDIENTS: ALCOHOL; PROPYLENE GLYCOL; WATER

84232-004

Active Ingredient(s)

Minoxidil 2% w/v

Purpose

HAIR REGROWTH TREATMENT

Use

to regrow hair on top of scalp (vertex only, see pictures on side of box)

Warnings

For external use only. For use by women FIammable: Keep away from fire or flame

Do not use

●Your degree of hair loss is different than that shown on the side of this carton, because this product may not work for you
●You have no family history of hair loss.
●Your hair loss is sudden and/or patchy.
●You do not know the reason for your hair loss.
●You are under 18 years of age. Do not use on babies and children.
●Your scalp is red, inflamed, infected, irritated, or painful.
●You use other medicines on the scalp.

When using this product.

●Do not apply on other parts of your body.
●Avoid contact with the eyes. In case of accidental contact, rinse eyes with cool tap water.
●Some people have experienced changes in hair color and/or texture.
●It takes time to regrow hair, results may occur at 2 months with twice a day usage. For some women, you may need to use this product for at least 4 months before you see results.
●The amount of hair regrowth is different for each person. This product will not work on all women.

Stop use

●Chest pain, rapid heartbeat, faintness, or dizziness occurs
●Sudden, unexplained weight gain occurs
●Your hands or feet swell
●Scalp rritation or redness occurs
●Unwanted facial hair growth occurs
●You do not see hair growth in 4 months
●May be harmful if used when pregnant or breast-feeding.
●Keep out of reach of children. If swallowed, get medical help or contact a Poison Control Center right away. .

Keep out of reach of children. If swallowed, get medical help or contact a Poison Control Center right away.

Directions

●Apply one mL. with dropper 2 times a day directly onto the scalp in the hair loss area.

●Using more or more often will not improve resufts.

●continued use is necessary to increase and keep your hair regrowth, or hair loss will begin again.

Other information

●See hair loss pictures on side of box.
●Before use, read all information on box and enclosed instructions.
●Keep the box, it contains important information.
●Hair regrowth has not been shown to last longer than 48 weeks in large clinical trials with continuous treatment with minoxidil topical
solution 2% for women.
●In clinical studies of mostly white women aged 18-45 with mild to moderate hair loss, 19% showed moderate hair regrowth after 8 months of using 2% minoxidil topical solution, compared to 7% with a placebo. Additionally, 40% had
minimal regrowth with minoxidil, while 33% saw minimal regrowth with the placebo.
●Store at 20° to 25°C (68° to 77°F). Keep cap tightly closed.

Inactive ingredients

alcohol, propylene glycol, purified water.